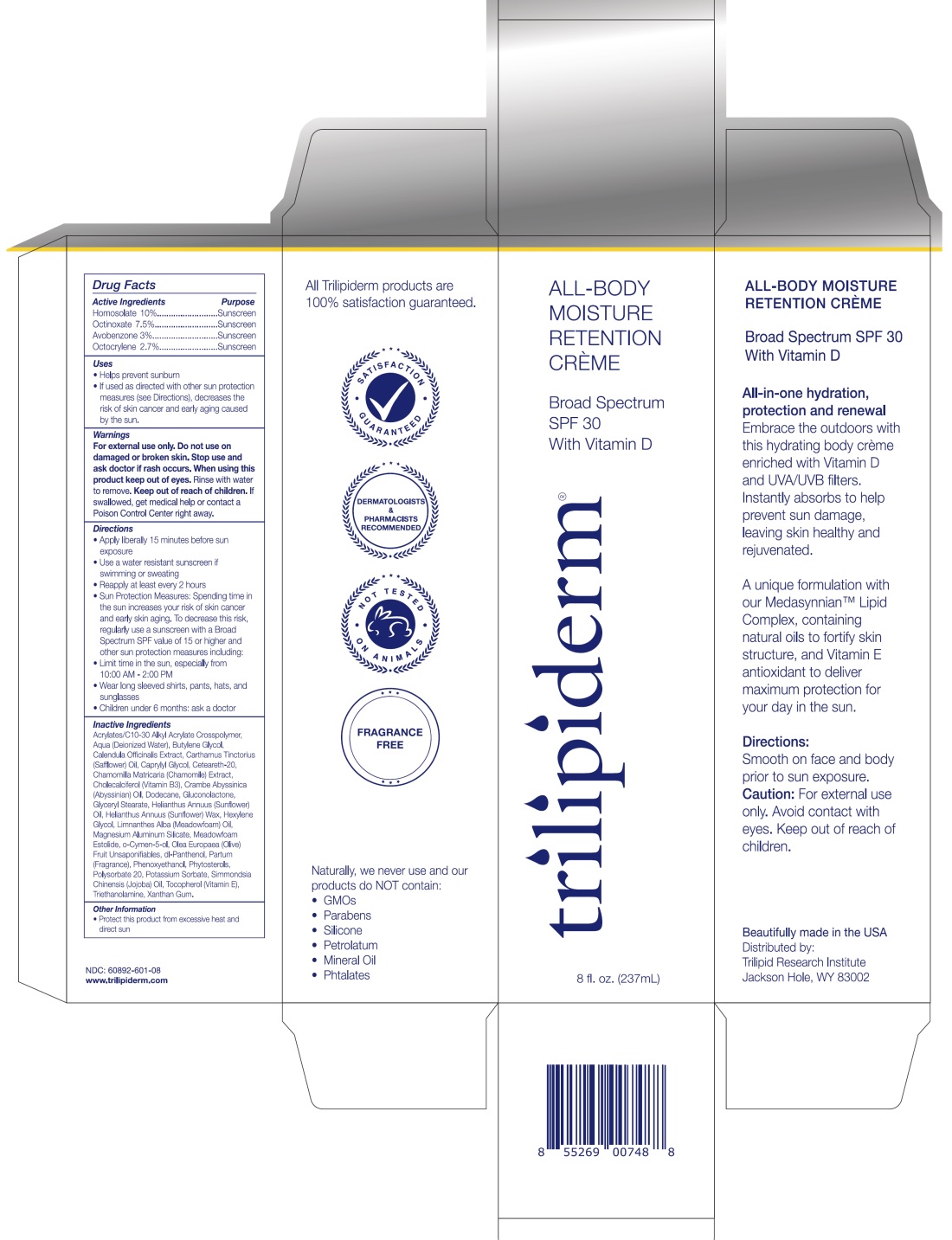 DRUG LABEL: TriLipiderm
NDC: 60892-601 | Form: CREAM
Manufacturer: TriLipid Research Institute, LLC
Category: otc | Type: HUMAN OTC DRUG LABEL
Date: 20251110

ACTIVE INGREDIENTS: AVOBENZONE 3 g/100 mL; OCTINOXATE 7.5 g/100 mL; HOMOSALATE 10 g/100 mL; OCTOCRYLENE 2.7 g/100 mL
INACTIVE INGREDIENTS: SAFFLOWER OIL; POLYOXYL 20 CETOSTEARYL ETHER; CHAMOMILE; HEXYLENE GLYCOL; MEADOWFOAM ESTOLIDE; OLEA EUROPAEA (OLIVE) OIL UNSAPONIFIABLES; PANTHENOL; CRAMBE HISPANICA SUBSP. ABYSSINICA WHOLE; POTASSIUM SORBATE; TOCOPHEROL; ACRYLATES/C10-30 ALKYL ACRYLATE CROSSPOLYMER (60000 MPA.S); MAGNESIUM ALUMINUM SILICATE; PHENOXYETHANOL; WATER; XANTHAN GUM; DODECANE; BUTYLENE GLYCOL; LIMNANTHES ALBA WHOLE; GLUCONOLACTONE; GLYCERYL MONOSTEARATE; SUNFLOWER OIL; JOJOBA OIL; TROLAMINE; POLYSORBATE 20; CHOLECALCIFEROL; CAPRYLYL GLYCOL; CALENDULA OFFICINALIS FLOWERING TOP

TriLipiderm Broad Spectrum SPF 30

Active Ingredients

Butyl Methoxydibenzoylmethane 3%, Ethylhexyl Methoxycinnamate 7.5%, Homosalate 10%, Octocrylene 2.7%

Purpose

Sunscreen

Uses

- Helps Prevent Sunburn

- If used as directed with other sun protection measures (see Directions), decreases the risk of skin cancer and early skin aging caused by the sun

Warnings

For External Use Only

Do Not Use

on Damaged or Broken Skin

Stop Use and Ask a Doctor

If Rash Occurs

When Using This Product

Keep Out Of Eyes. Rinse with water to remove

Keep Out of Reach of Children.

If swallowed get medical help or contact a Poison Control Center right away

Directions:

- Apply liberally 15 minutes before sun exposure
- Use a water resistant sunscreen if swimming or sweating
- Reapply at least every 2 hours
- Children under 6 months: ask a doctor
- Sun Protection Measures. Spending time in the sun increases your risk of skin cancer and early skin aging. To decrease this risk, regularly use a sunscreen with a Broad Spectrum SPF value of 15 or higher and other sun protection measures including:
- Limit time in the sun, especially from 10:00 AM – 2:00 PM
- Wear long sleeved shirts, pants, hats, and sunglasses

Inactive Ingredients:

Acrylates/C10-30 Alkyl Acrylate Crosspolymer, Aqua (Deionized Water), Butylene Glycol, Calendula Officinalis Extract, Carthamus Tinctorius (Safflower) Oil, Caprylyl Glycol, Ceteareth-20, Chamomilla Matricaria (Chamomile) Extract, Cholecalciferol (Vitamin B3), Crambe Abyssinica (Abyssinian) Oil, Dodecane, Gluconolactone, Glyceryl Stearate, Helianthus Annuus (Sunflower) Oil, Helianthus Annuus (Sunflower) Wax, Hexylene Glycol, Limnanthes Alba (Meadowfoam) Oil, Magnesium Aluminum Silicate, Meadowfoam Estolide, o-Cymen-5-ol, Olea Europeaea (Olive) Fruit Unsaponifiables, dl-Panthenol, Partum (Fragrance), Phenoxyethanol, Phytosterols, Polysorbate 20, Potassium Sorbate, Simmondsia Chinensis (Jojoba) Oil, Tocopherol (Vitamin E), Triethanolamine, Xanthan Gum.

Other Information

- Protect this product from excessive heat and direct sun

Made in the USA * Distributed by:

Trilipid Research Institute LLC

Jackson, WY 83002

PACKAGE LABEL

All-Body Moisture Retention Creme Broad Spectrum SPF 30